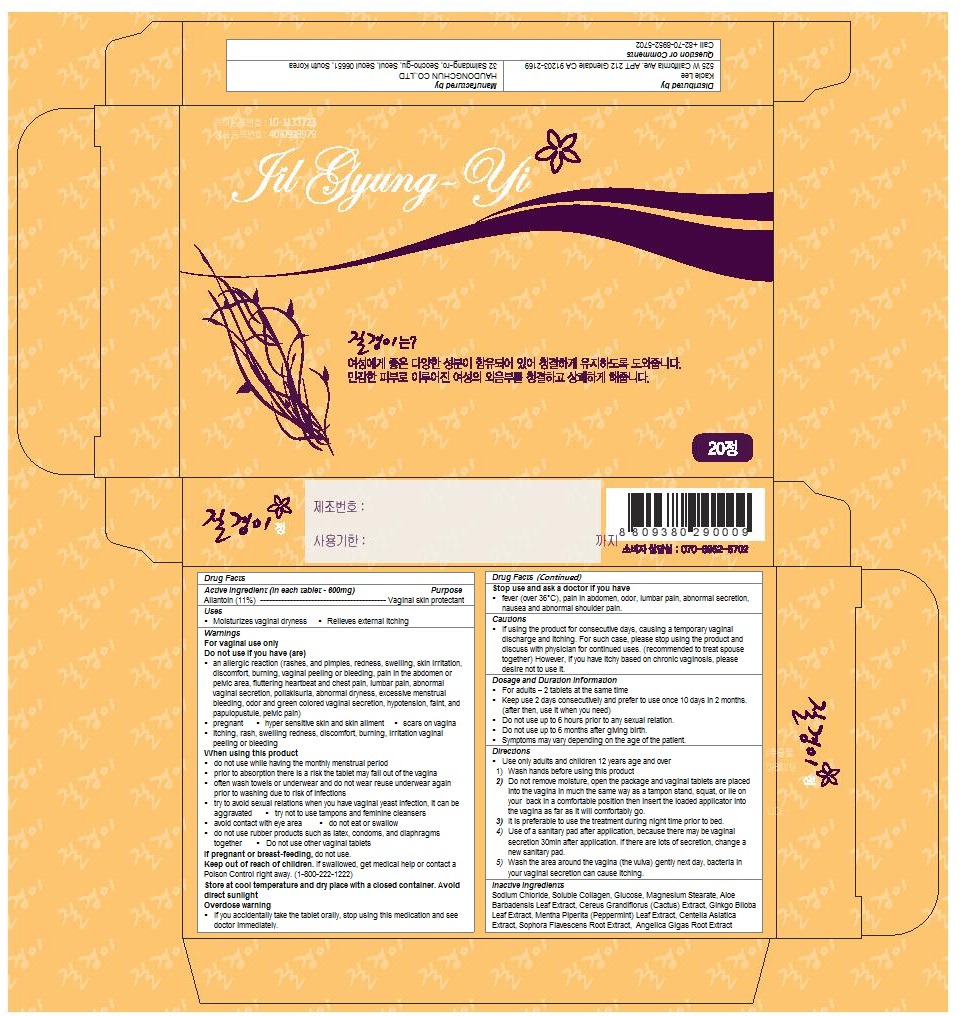 DRUG LABEL: Jilgyungyi (20 Tablets)
NDC: 55618-2004 | Form: TABLET
Manufacturer: Haudongchun Co., Ltd.
Category: otc | Type: HUMAN OTC DRUG LABEL
Date: 20160711

ACTIVE INGREDIENTS: ALLANTOIN 0.11 1/600 mg
INACTIVE INGREDIENTS: Sodium Chloride; .ALPHA.-D-GLUCOPYRANOSE; MAGNESIUM STEARATE; ALOE VERA LEAF; GINKGO; MENTHA PIPERITA LEAF; CENTELLA ASIATICA; SOPHORA FLAVESCENS ROOT; ANGELICA GIGAS ROOT

Jilgyungyi (20 Tablets)